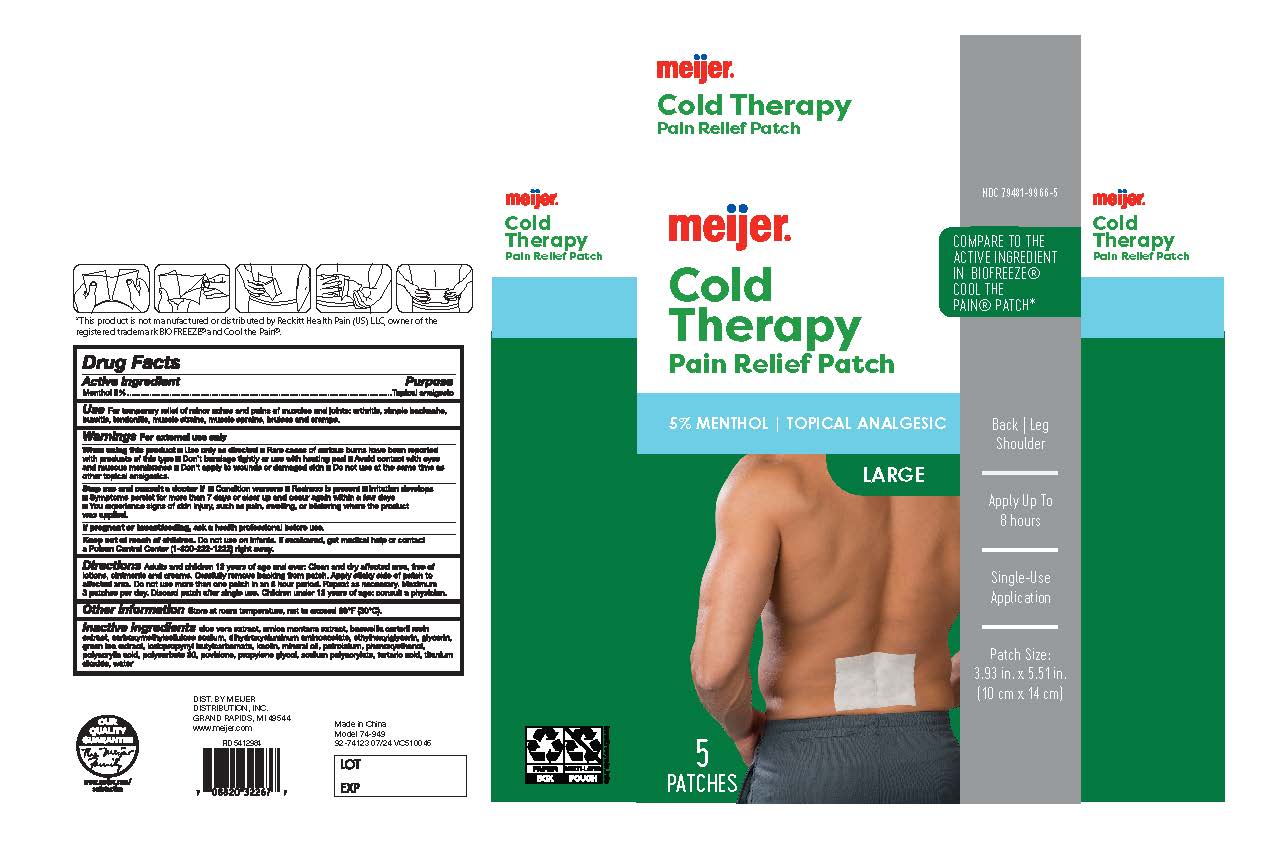 DRUG LABEL: Meijer Cold Therapy Pain Relieving
NDC: 79481-9966 | Form: PATCH
Manufacturer: Meijer Inc
Category: otc | Type: HUMAN OTC DRUG LABEL
Date: 20240808

ACTIVE INGREDIENTS: MENTHOL 5 g/100 g
INACTIVE INGREDIENTS: DIHYDROXYALUMINUM AMINOACETATE; PROPYLENE GLYCOL; BOSWELLIA SERRATA RESIN OIL; POLYACRYLIC ACID (8000 MW); WATER; MINERAL OIL; POVIDONE; PHENOXYETHANOL; KAOLIN; TITANIUM DIOXIDE; PETROLATUM; GLYCERIN; CARBOXYMETHYLCELLULOSE SODIUM; TARTARIC ACID; IODOPROPYNYL BUTYLCARBAMATE; ETHYLHEXYLGLYCERIN; POLYSORBATE 80; ALOE VERA LEAF; ARNICA MONTANA FLOWER; SODIUM POLYACRYLATE (8000 MW); GREEN TEA LEAF

Meijer Cold Therapy Pain Relieving Patch, 5 Count

Active Ingredient

Menthol 5%

Purpose

Topical Analgesic

Use

Use For temporary relief of minor aches and pains of muscles and joints: arthritis, simple backache, bursitis, tendonitis, muscle strains, muscle sprains, bruises, and cramps.

Warnings

For External Use Only

When using this product

■ Use only as directed

■Rare cases of serious burns have been reported with products of this type

■Don't bandage tightly or use with heating pad

■Avoid contact with eyes and mucous membranes

■Don't apply to wounds or damaged skin

■Do not use at the same time as other topical analgesics.

Stop use and Consult a doctor if

■ Condition worsens

■ Redness is present

■ Irritation develops
■ Symptoms persist for more than 7 days or clear up and occur again within a few days
■ You experience signs of skin injury, such as pain, swelling, or blistering where the product was applied.

If pregnant or breastfeeding

ask a health professional before use

Keep out of reach of children. Do not use on infants. If swallowed, get medical help or contact a Poison Control Center (1-800-222-1222) right away.

Directions

Directions Adults and children 12 years of age and over: Clean and dry affected area, free of lotions, ointments, and creams. Carefully remove backing from patch. Apply sticky side of patch to affected area. Do not use more than one patch in an 8 hour period. Repeat as necessary. Maximum 3 patches per day. Discard patch after single use. Children under 12 years of age: consult a physician.

Other Information

Store at room temperature, not to exceed 86 F (30C)

Inactive Ingredients

aloe vera extract, arnica montana extract, boswellia carterii resin extract, carboxymethylcellulose sodium, dihydroxyaluminum aminoacetate, ethylhexylglycerin, glycerin, green tea extract, iodopropynyl butylcarbamate, kaolin, mineral oil, petrolatum, phenoxyethanol, polyacrylic acid, polysorbate 80, povidone, propylene glycol, sodium polyacrylate, tartaric acid, titanium dioxide, water